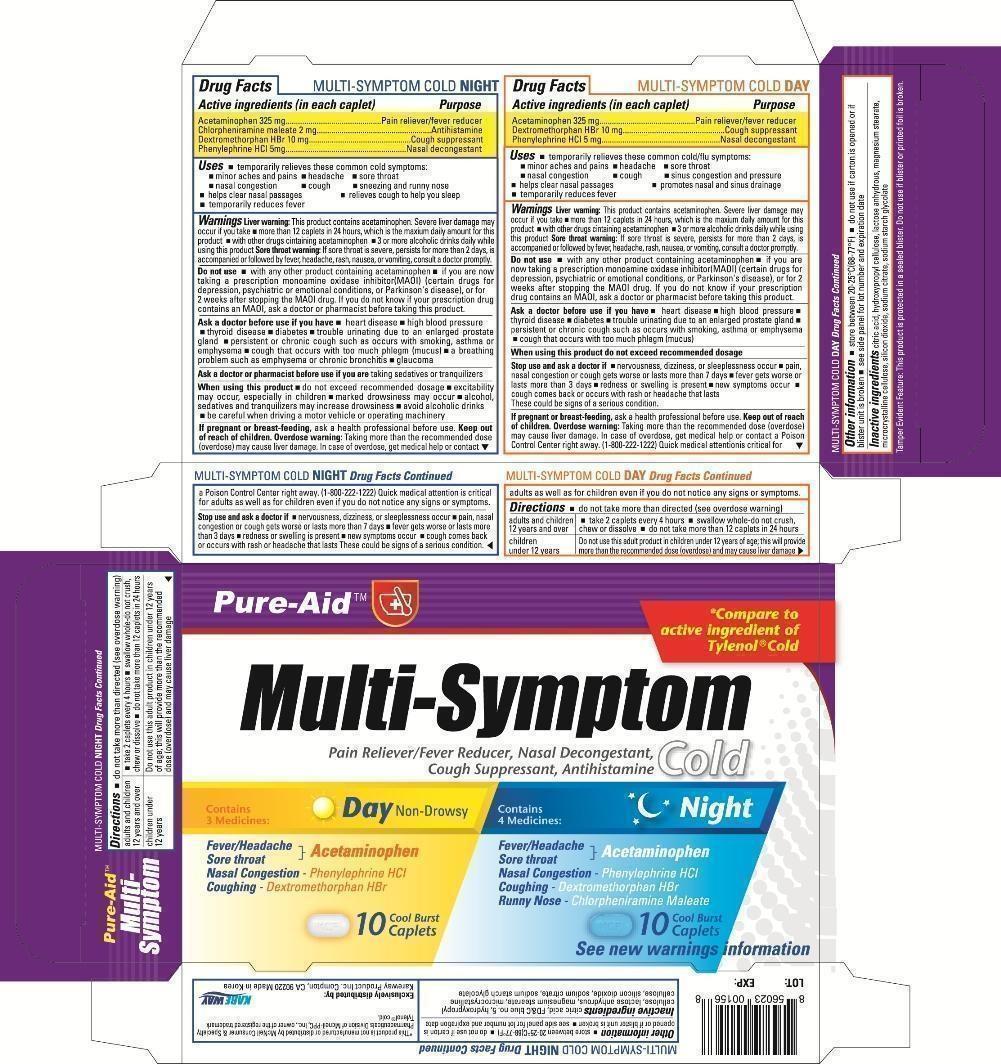 DRUG LABEL: Multi Sympton Cold Day Night
NDC: 67510-0156 | Form: KIT | Route: ORAL
Manufacturer: Kareway Product, Inc.
Category: otc | Type: HUMAN OTC DRUG LABEL
Date: 20130216

ACTIVE INGREDIENTS: ACETAMINOPHEN 325 mg/1 1; CHLORPHENIRAMINE MALEATE 2 mg/1 1; DEXTROMETHORPHAN HYDROBROMIDE 10 mg/1 1; PHENYLEPHRINE HYDROCHLORIDE 5 mg/1 1; ACETAMINOPHEN 325 mg/1 1; DEXTROMETHORPHAN HYDROBROMIDE 10 mg/1 1; PHENYLEPHRINE HYDROCHLORIDE 5 mg/1 1
INACTIVE INGREDIENTS: CITRIC ACID MONOHYDRATE; HYDROXYPROPYL CELLULOSE; ANHYDROUS LACTOSE; MAGNESIUM STEARATE; CELLULOSE, MICROCRYSTALLINE; SILICON DIOXIDE; SODIUM CITRATE; SODIUM STARCH GLYCOLATE TYPE A CORN; CITRIC ACID MONOHYDRATE; HYDROXYPROPYL CELLULOSE; ANHYDROUS LACTOSE; MAGNESIUM STEARATE; CELLULOSE, MICROCRYSTALLINE; SILICON DIOXIDE; SODIUM CITRATE; SODIUM STARCH GLYCOLATE TYPE A CORN

Drug Facts

Active ingredients for Night(in each tablet)

Acetaminophen 325 mg

Chlorpheniramine maleate 2 mg

Dextromethorphan HBr 10 mg

Phenylephrine HCl 5 mg

Active ingredients for Day(in each tablet)

Acetaminophen 325 mg

Dextromethorphan HBr 10 mg

Phenylephrine HCl 5 mg

Purpose for Night

Pain reliever/fever reducer

Antihistamine

Cough suppressant

Nasal decongestant

Purpose for Day

Pain reliever/fever reducer

Cough suppressant

Nasal decongestant

Uses

- temporarily relieves these common cold symptoms:
- minor aches and pains
- headache
- sore throat
- nasal congestion
- cough
- sneezing and runny nose (Night only)
- sinus congestion and pressure (Day only)
- helps clear nasal passages
- relieves cough to help you sleep (Night only)
- promotes nasal and sinus drainage (Day only)
- temporarily reduces fever

Warnings

Alcohol warning:If you consume 3 or more alcoholic drinks every day, ask your doctor whether you should take acetaminophen or other pain relievers or fever reducers. Acetaminophen may cause liver damage.Sore throat warning: If sore throat is severe, persists for more than 2 days, is accompanied or followed by fever, headache, rash, nausea, or vomiting, consult a doctor promptly.

Do not use

- with any other product containing acetaminophen
- if you are now taking a prescription monoamine oxidase inhibitor (MAOI) (certain drugs for depression, psychiatric or emotional conditions, or Parkinson's disease), or for 2 weeks after stopping the MAOI drug. If you do not know if you prescription drug contains an MAOI, ask a doctor or pharmacist before taking this product.

Ask a doctor before use if you have

- heart disease
- high blood pressure
- thyroid disease
- diabetes
- trouble urinating due to an enlarged prostate gland
- persistent or chronic cough such as occurs with smoking, asthma or emphysema
- cough that occurs with too much phlegm (mucus)
- a breathing problem such as emphysema or chronic bronchitis (Night only)
- glaucoma (Night only)

Ask a doctor or pharmacist before use if you are (Night only)

taking sedatives or tranquilizers (Night only)

When using this product

- do not exceed recommended dosage
- excitability may occur, especially in children (Night only)
- marked drowsiness may occur (Night only)
- alcohol, sedatives and tranquilizers may increase drowsiness (Night only)
- avoid alcoholic drinks (Night only)
- be careful when driving a motor vehicle or operating machinery (Night only)

If pregnant or breastfeeding,

ask a health professional before use.

Keep out of reach of children.

Enter section text here

Overdose warning:

Taking more than the recommended dose (overdose) may cause liver damage. In case of overdose, get medical help or contact a Poison Control Center right away. (1-800-222-1222) Quick medical attention is critical for adults as well as for children even if you do not notice any signs or symptoms.

Stop use and ask a doctor if

- nervousness, dizziness, or sleeplessness occur
- pain, nasal congestion or cough gets worse or lasts more than 7 days
- fever gets worse or lasts more than 3 days
- redness or swelling is present
- new symptoms occur
- cough comes back or occurs with rash or headache that lasts

These could be signs of a serious condition.

Directions

- do not take more than directed (see overdose warning)

adults and children 12 years and over | - take 2 tablets every 4 hours - swallow whole - do not crush, chew or dissolve - do not take more than 12 tablets in 24 hours
children under 12 years | Do not use this adult product in children under 12 years of age; this will provide more than the recommended dose (overdose) and may cause liver damage

Other information

- store between 20-25°C (68-77°F)
- do not use if carton is opened or if blister unit is broken
- see side panel for lot number and expiration date

Inactive ingredients

microcrystalline cellulose, lactose, hydroxypropyl cellulose, sodium starch glycolate, sillicon dioxide, magnesium stearate, hypromellose (Night only), bleu no.1 (Night only), titanium dioxide (Night only), polyethylene glycol (Night only), anhydrous citric acid, sodium citrate, ethanol, FDC Yellow no.5 (Day only),